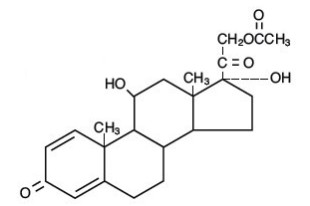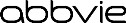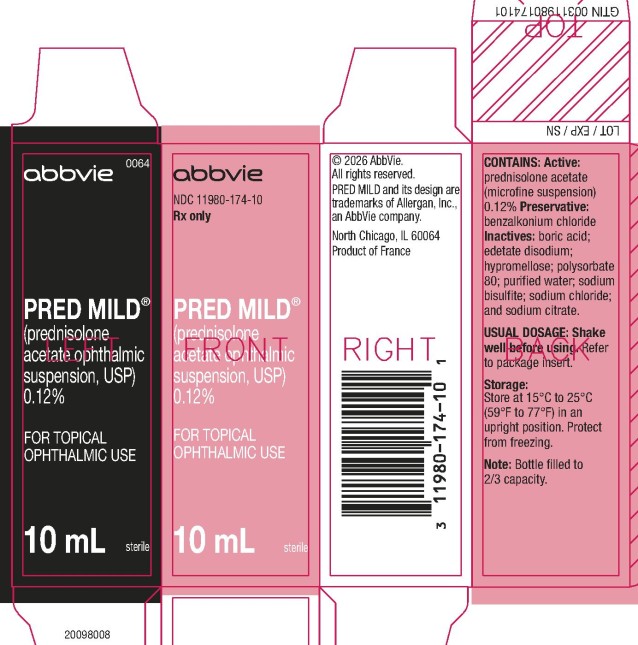 DRUG LABEL: PRED MILD
NDC: 11980-174 | Form: SUSPENSION/ DROPS
Manufacturer: Allergan, Inc.
Category: prescription | Type: HUMAN PRESCRIPTION DRUG LABEL
Date: 20251125

ACTIVE INGREDIENTS: PREDNISOLONE ACETATE 1.2 mg/1 mL
INACTIVE INGREDIENTS: BENZALKONIUM CHLORIDE; BORIC ACID; EDETATE DISODIUM; HYPROMELLOSE, UNSPECIFIED; POLYSORBATE 80; WATER; SODIUM BISULFITE; SODIUM CHLORIDE; SODIUM CITRATE

PRED MILD®
(prednisolone acetate ophthalmic suspension, USP) 0.12%
sterile

DESCRIPTION

PRED MILD® (prednisolone acetate ophthalmic suspension, USP) 0.12% is a sterile, topical anti-inflammatory agent for ophthalmic use. Its chemical name is 11ß,17, 21-Trihydroxypregna-1,4-diene-3, 20-dione 21-acetate and it has the following structure:

Structural Formula:

prednisolone acetate

Active: prednisolone acetate (microfine suspension) 0.12%.

Inactives: benzalkonium chloride as preservative; boric acid; edetate disodium; hypromellose; polysorbate 80; purified water; sodium bisulfite; sodium chloride; and sodium citrate. The pH during its shelf life ranges from 5.0 - 6.0.

CLINICAL PHARMACOLOGY

Prednisolone acetate is a glucocorticoid that, on the basis of weight, has 3 to 5 times the anti-inflammatory potency of hydrocortisone. Glucocorticoids inhibit the edema, fibrin deposition, capillary dilation, and phagocytic migration of the acute inflammatory response, as well as capillary proliferation, deposition of collagen, and scar formation.

INDICATIONS AND USAGE

PRED MILD® is indicated for the treatment of mild to moderate noninfectious allergic and inflammatory disorders of the lid, conjunctiva, cornea, and sclera (including chemical and thermal burns).

CONTRAINDICATIONS

PRED MILD® suspension is contraindicated in acute untreated purulent ocular infections, in most viral diseases of the cornea and conjunctiva including epithelial herpes simplex keratitis (dendritic keratitis), vaccinia, and varicella, and also in mycobacterial infection of the eye and fungal diseases of ocular structures. PRED MILD® suspension is also contraindicated in individuals with known or suspected hypersensitivity to any of the ingredients of this preparation and to other corticosteroids.

WARNINGS

Prolonged use of corticosteroids may result in posterior subcapsular cataract formation and may increase intraocular pressure in susceptible individuals, resulting in glaucoma with damage to the optic nerve, defects in visual acuity and fields of vision. Prolonged use may also suppress the host immune response and thus increase the hazard of secondary ocular infections.

If this product is used for 10 days or longer, intraocular pressure should be routinely monitored even though it may be difficult in children and uncooperative patients. Steroids should be used with caution in the presence of glaucoma. Intraocular pressure should be checked frequently.

Various ocular diseases and long-term use of topical corticosteroids have been known to cause corneal and scleral thinning. Use of topical corticosteroids in the presence of thin corneal or scleral tissue may lead to perforation.

Acute purulent infections of the eye may be masked or activity enhanced by the presence of corticosteroid medication.

The use of steroids after cataract surgery may delay healing and increase the incidence of bleb formation.

Use of ocular steroids may prolong the course and may exacerbate the severity of many viral infections of the eye (including herpes simplex). Employment of a corticosteroid medication in the treatment of patients with a history of herpes simplex requires great caution; frequent slit lamp microscopy is recommended.

PRED MILD® suspension contains sodium bisulfite, a sulfite that may cause allergic-type reactions, including anaphylactic symptoms and life-threatening or less severe asthmatic episodes in certain susceptible people. The overall prevalence of sulfite sensitivity in the general population is unknown and probably low. Sulfite sensitivity is seen more frequently in asthmatic than in non-asthmatic people.

PRECAUTIONS

General

The initial prescription and renewal of the medication order of PRED MILD® should be made by a physician only after examination of the patient with the aid of magnification, such as slit lamp biomicroscopy, and, where appropriate, fluorescein staining. If signs and symptoms fail to improve after 2 days, the patient should be re-evaluated.

As fungal infections of the cornea are particularly prone to develop coincidentally with long-term local corticosteroid applications, fungal invasion should be suspected in any persistent corneal ulceration where a corticosteroid has been used or is in use. Fungal cultures should be taken when appropriate.

Information for Patients

Advise patients that if eye inflammation or pain persists longer than 48 hours or becomes aggravated, they should consult a physician.

Advise patients that to prevent eye injury or contamination, care should be taken to avoid touching the bottle tip to eyelids or to any other surface. The use of this bottle by more than one person may spread infection. Keep bottle tightly closed when not in use. Keep out of the reach of children.

Advise patients that PRED MILD® suspension contains benzalkonium chloride, which may be absorbed by soft contact lenses. Contact lenses should be removed prior to application of PRED MILD® and may be reinserted 15 minutes following its administration.

Carcinogenesis, Mutagenesis, Impairment of Fertility

No studies have been conducted in animals or in humans to evaluate the potential of these effects.

Pregnancy

Prednisolone has been shown to be teratogenic in mice when given in doses 1-10 times the human dose. Dexamethasone, hydrocortisone, and prednisolone were ocularly applied to both eyes of pregnant mice five times per day on days 10 through 13 of gestation. A significant increase in the incidence of cleft palate was observed in the fetuses of the treated mice. There are no adequate well-controlled studies in pregnant women. Prednisolone should be used during pregnancy only if the potential benefit justifies the potential risk to the fetus.

Nursing Mothers

It is not known whether topical ophthalmic administration of corticosteroids could result in sufficient systemic absorption to produce detectable quantities in breast milk. Systemically administered corticosteroids appear in human milk and could suppress growth, interfere with endogenous corticosteroid production, or cause other untoward effects. Because of the potential for serious adverse reactions in nursing infants from prednisolone, a decision should be made whether to discontinue nursing or to discontinue the drug, taking into account the importance of the drug to the mother.

Pediatric Use

The safety and effectiveness in pediatric patients have been established. Use in pediatric patients is supported by evidence from adequate and well-controlled studies of prednisolone acetate ophthalmic suspension in adults with additional data in pediatric patients.

Geriatric Use

No overall differences in safety or effectiveness have been observed between elderly and younger patients.

ADVERSE REACTIONS

The following adverse reactions have been identified during use of PRED MILD®. Because reactions are reported voluntarily from a population of uncertain size, it is not always possible to reliably estimate their frequency or establish a causal relationship to drug exposure.

Adverse reactions include elevation of intraocular pressure (IOP) with possible development of glaucoma and infrequent optic nerve damage, posterior subcapsular cataract formation, and delayed wound healing.

The development of secondary ocular infection (bacterial, fungal, and viral) has occurred. Fungal and viral infections of the cornea are particularly prone to develop coincidentally with long-term applications of steroids. The possibility of fungal invasion should be considered in any persistent corneal ulceration where steroid treatment has been used (see PRECAUTIONS).

Other adverse reactions reported with the use of prednisolone acetate ophthalmic suspension include: allergic reactions; dysgeusia; eye pain; foreign body sensation; headache; pruritus; rash; transient burning and stinging upon instillation and other minor symptoms of ocular irritation; urticaria; and visual disturbance (blurry vision).

Keratitis, conjunctivitis, corneal ulcers, mydriasis, conjunctival hyperemia, loss of accommodation and ptosis have occasionally been reported following local use of corticosteroids. Corticosteroid-containing preparations have also been reported to cause acute anterior uveitis and perforation of the globe.

OVERDOSAGE

Overdosage will not ordinarily cause acute problems. If accidentally ingested, drink fluids to dilute.

DOSAGE AND ADMINISTRATION

Shake well before using. Instill one to two drops into the conjunctival sac two to four times daily. During the initial 24 to 48 hours, the dosing frequency may be increased if necessary. Care should be taken not to discontinue therapy prematurely.

If signs and symptoms fail to improve after 2 days, the patient should be re-evaluated (see PRECAUTIONS).

HOW SUPPLIED

PRED MILD® (prednisolone acetate ophthalmic suspension, USP) 0.12% is supplied sterile in opaque white LDPE plastic bottles with droppers with pink high impact polystyrene (HIPS) caps as follows:

5 mL in 10 mL bottle - NDC 11980-174-05

10 mL in 15 mL bottle - NDC 11980-174-10

Storage: Store at 15°C to 25°C (59°F to 77°F) in an upright position. Protect from freezing.

Revised: 11/2025

Distributed by:
AbbVie, Inc.
North Chicago, IL 60064

© 2025 AbbVie. All rights reserved.
Pred Mild and its design are trademarks of Allergan, Inc., an AbbVie company.

20095922

PRINCIPAL DISPLAY PANEL

NDC 11980-174-10
Rx Only
PRED MILD®
(prednisolone
acetate ophthalmic
suspension, USP)
0.12%
FOR TOPICAL
OPHTHALMIC USE
sterile
10 mL